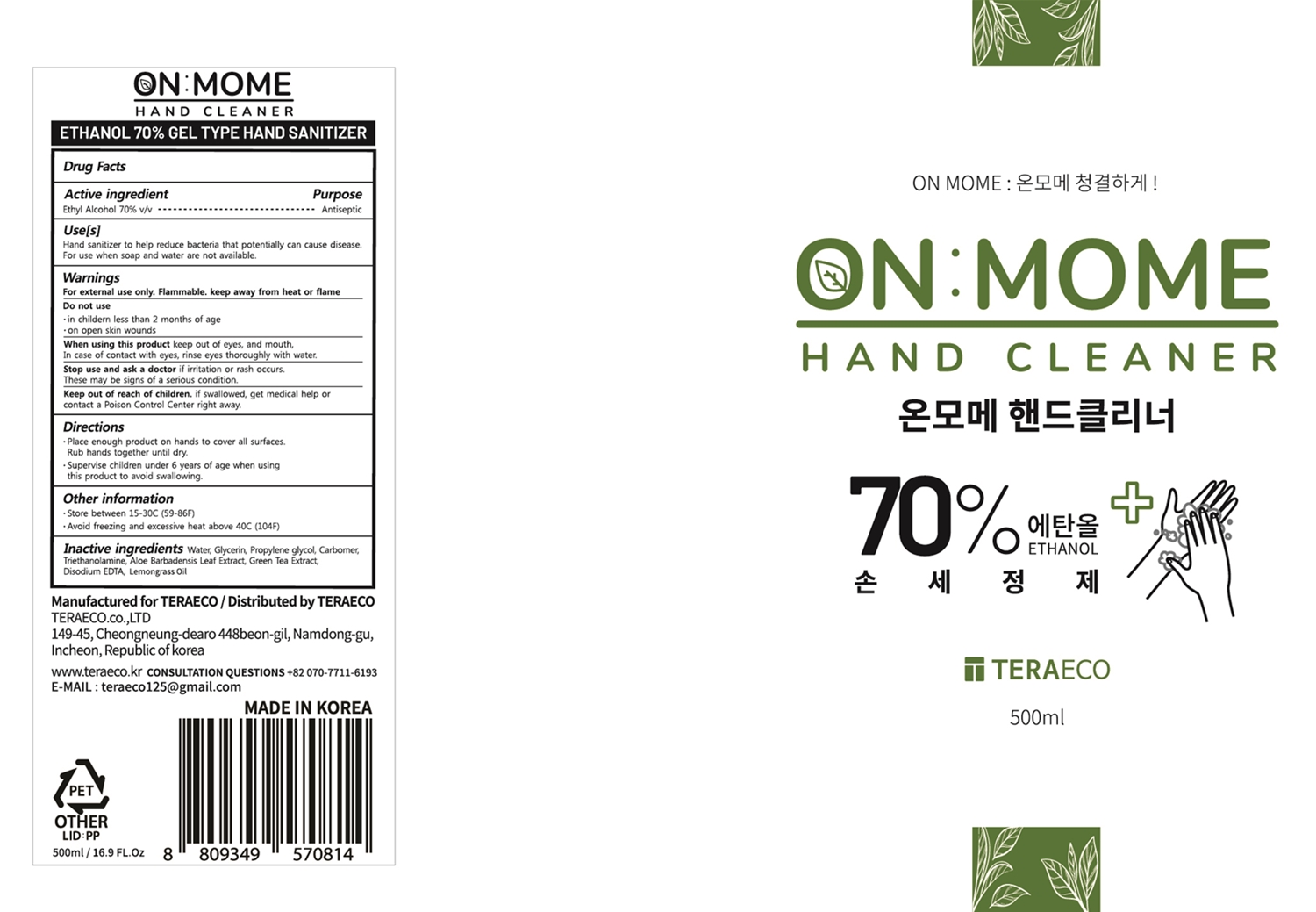 DRUG LABEL: ONMOME HAND CLEANER
NDC: 79545-201 | Form: LIQUID
Manufacturer: TERAECO., LTD
Category: otc | Type: HUMAN OTC DRUG LABEL
Date: 20200710

ACTIVE INGREDIENTS: ALCOHOL 70 mL/100 mL
INACTIVE INGREDIENTS: PROPYLENE GLYCOL; GREEN TEA LEAF; TROLAMINE; EDETATE DISODIUM ANHYDROUS; WATER; GLYCERIN; CARBOMER HOMOPOLYMER, UNSPECIFIED TYPE; ALOE VERA LEAF; WEST INDIAN LEMONGRASS OIL

79545-201

Active ingredient

Ethyl Alcohol 70%

Purpose

Antiseptic

Use

Hand sanitizer to help reduce bacteria that potentially can cause disease. For use when soap and water are not available.

Warnings

For external use only. Flammable. Keep away from heat or flame.

Do not use

in childern less than 2 months of age

on open skin wounds

When using this product

keep out of eyes, and mouth, In case of contact with eyes, rinse eyes thoroughly with water.

Stop use and ask a doctor

if irritation or rash occurs. These may be signs of a serious condition.

Keep out of reach of children.

if swallowed, get medical help or contact a Poison Control Center right away.

Directions

Place enough product on hands to cover all surfaces. Rub hands together until dry.

Supervise children under 6 years of age when using this product to avoid swallowing.

Other information

Store between 15-30C (59-86F)

Avoid freezing and excessive heat above 40C (104F)

Inactive ingredients

Water, Glycerin, Propylene Glycol, Carbomer, Triethanolamine, Aloe Barbadensis Leaf Extract, Green Tea Extract, Disodium EDTA, Lemongrass Oil